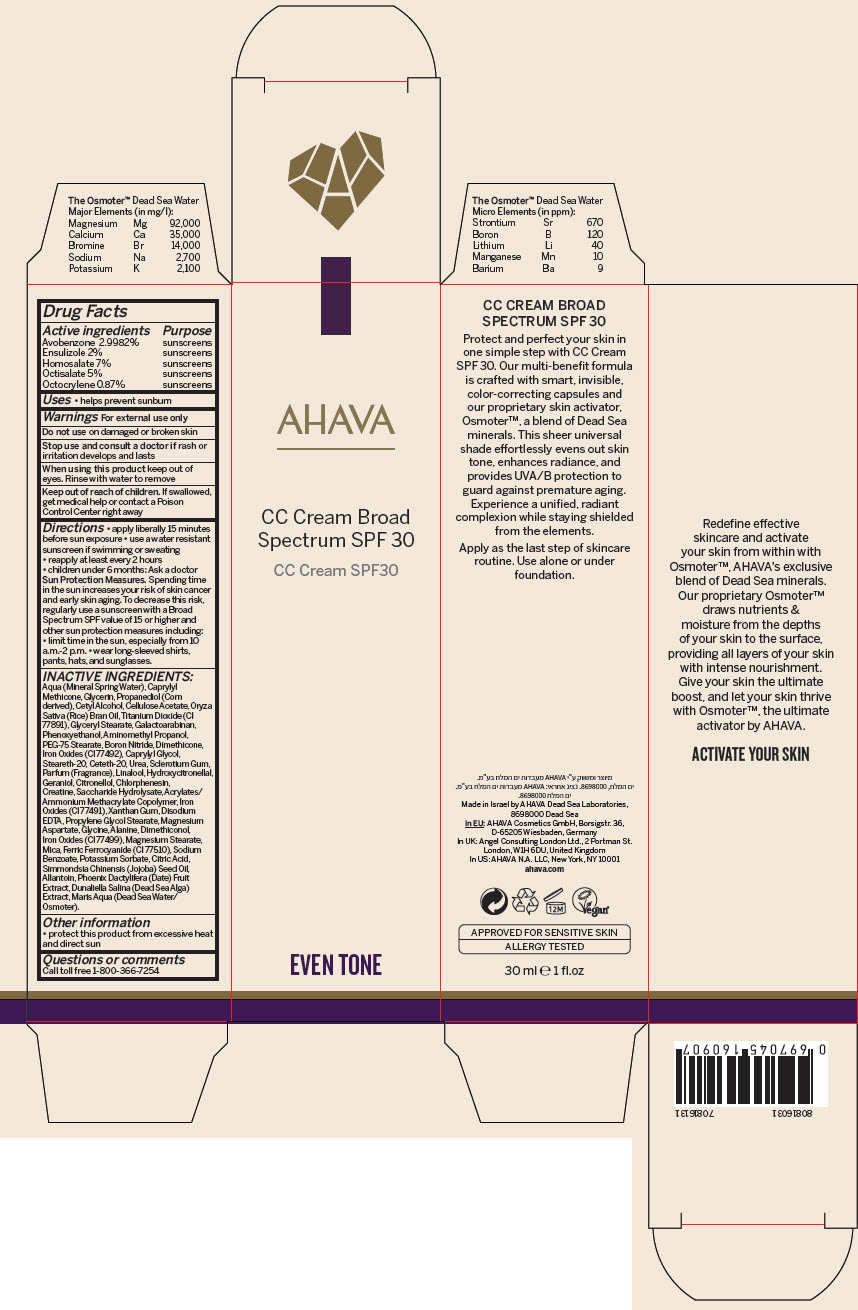 DRUG LABEL: AHAVA  CC SPF 30
NDC: 60289-304 | Form: CREAM
Manufacturer: AHAVA - Dead Sea Laboratories Ltd
Category: otc | Type: HUMAN OTC DRUG LABEL
Date: 20241204

ACTIVE INGREDIENTS: Avobenzone 29.982 mg/1 mL; Ensulizole 20 mg/1 mL; Homosalate 70 mg/1 mL; Octisalate 50 mg/1 mL; Octocrylene 8.7 mg/1 mL
INACTIVE INGREDIENTS: Water; CAPRYLYL TRISILOXANE; Glycerin; Propanediol; Cetyl Alcohol; Cellulose Acetate; RICE BRAN OIL; Titanium Dioxide; Glyceryl Monostearate; Galactoarabinan; Phenoxyethanol; Aminomethylpropanol; PEG-75 STEARATE; Boron Nitride; Dimethicone; FERRIC OXIDE YELLOW; Caprylyl Glycol; Steareth-20; Ceteth-20; Urea; BETASIZOFIRAN; LINALOOL, (+/-)-; Hydroxycitronellal; Geraniol; .BETA.-CITRONELLOL, (R)-; Chlorphenesin; Creatine; INVERT SUGAR; FERRIC OXIDE RED; Xanthan Gum; EDETATE DISODIUM; PROPYLENE GLYCOL MONOSTEARATE; Magnesium Aspartate; Glycine; Alanine; FERROSOFERRIC OXIDE; MAGNESIUM STEARATE; MICA; FERRIC AMMONIUM FERROCYANIDE; SODIUM BENZOATE; POTASSIUM SORBATE; CITRIC ACID MONOHYDRATE; JOJOBA OIL; ALLANTOIN; Dunaliella Salina; Date

AHAVA CC SPF 30

Drug Facts

ACTIVE INGREDIENT

Active ingredients | Purpose
Avobenzone 2.9982% | sunscreens
Ensulizole 2% | sunscreens
Homosalate 7% | sunscreens
Octisalate 5% | sunscreens
Octocrylene 0.87% | sunscreens

Uses

- helps prevent sunburn

Warnings

For external use only

Do not use on damaged or broken skin

Stop use and consult a doctor if rash or irritation develops and lasts

When using this product keep out of eyes. Rinse with water to remove

Keep out of reach of children. If swallowed, get medical help or contact a Poison Control Center right away

Directions

- apply liberally 15 minutes before sun exposure
- use a water resistant sunscreen if swimming or sweating
- reapply at least every 2 hours
- children under 6 months: Ask a doctor

Sun Protection Measures

Spending time in the sun increases your risk of skin cancer and early skin aging. To decrease this risk, regularly use a sunscreen with a Broad Spectrum SPF value of 15 or higher and other sun protection measures including:

- limit time in the sun, especially from 10 a.m.-2 p.m.
- wear long-sleeved shirts, pants, hats, and sunglasses.

INACTIVE INGREDIENTS

Aqua (Mineral Spring Water), Caprylyl Methicone, Glycerin, Propanediol (Corn derived), Cetyl Alcohol, Cellulose Acetate, Oryza Sativa (Rice) Bran Oil, Titanium Dioxide (CI 77891), Glyceryl Stearate, Galactoarabinan, Phenoxyethanol, Aminomethyl Propanol, PEG-75 Stearate, Boron Nitride, Dimethicone, Iron Oxides (CI 77492), Caprylyl Glycol, Steareth-20, Ceteth-20, Urea, Sclerotium Gum, Parfum (Fragrance), Linalool, Hydroxycitronellal, Geraniol, Citronellol, Chlorphenesin, Creatine, Saccharide Hydrolysate, Acrylates/Ammonium Methacrylate Copolymer, Iron Oxides (CI 77491), Xanthan Gum, Disodium EDTA, Propylene Glycol Stearate, Magnesium Aspartate, Glycine, Alanine, Dimethiconol, Iron Oxides (CI 77499), Magnesium Stearate, Mica, Ferric Ferrocyanide (CI 77510), Sodium Benzoate, Potassium Sorbate, Citric Acid, Simmondsia Chinensis (Jojoba) Seed Oil, Allantoin, Phoenix Dactylifera (Date) Fruit Extract, Dunaliella Salina (Dead Sea Alga) Extract, Maris Aqua (Dead Sea Water/Osmoter).

Other information

- protect this product from excessive heat and direct sun

Questions or comments

Call toll free 1-800-366-7254

PRINCIPAL DISPLAY PANEL - 30 ml Tube Carton

AHAVA

CC Cream Broad
Spectrum SPF 30

CC Cream SPF30

EVEN TONE